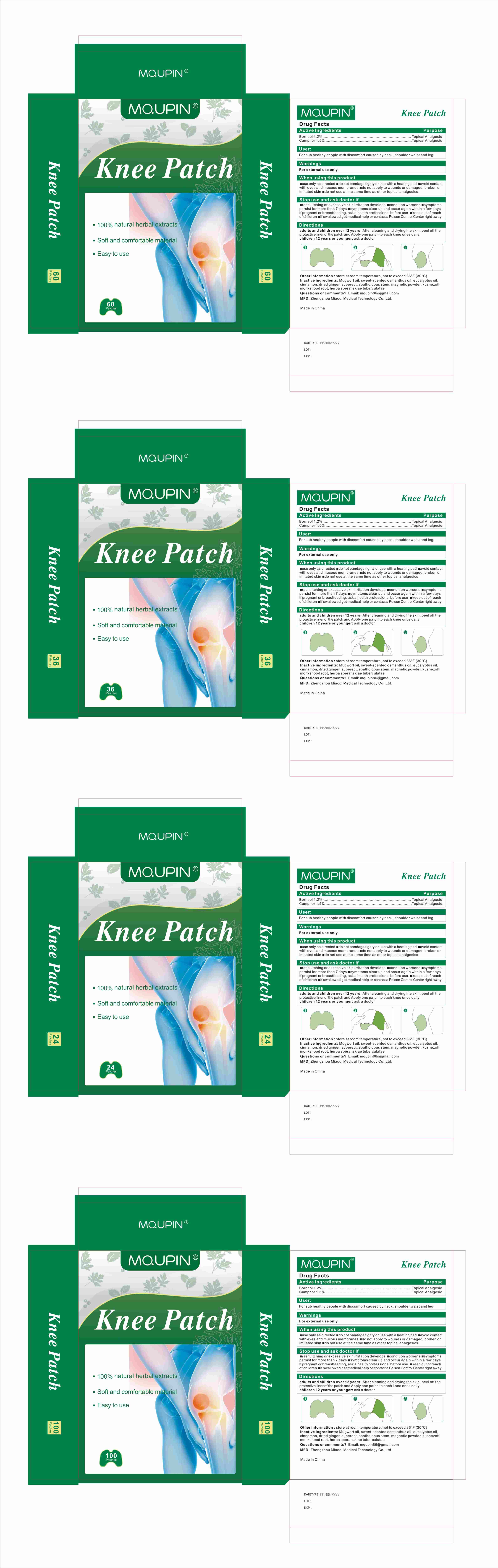 DRUG LABEL: MQUPIN Knee Patch
NDC: 83781-011 | Form: PATCH
Manufacturer: Zhengzhou Miaoqi Medical Technology Co., Ltd.
Category: otc | Type: HUMAN OTC DRUG LABEL
Date: 20250610

ACTIVE INGREDIENTS: CAMPHOR (SYNTHETIC) 1.5 g/100 1; BORNEOL 1.2 g/100 1
INACTIVE INGREDIENTS: ACONITUM NAPELLUS ROOT; SPATHOLOBUS SUBERECTUS WHOLE; GINGER; CINNAMON; FERROSOFERRIC OXIDE; ACONITUM KUSNEZOFFII LEAF; ARTEMISIA VULGARIS OIL; EUCALYPTUS OIL; 3,3-DIMETHYLCYCLOHEXYL METHYL KETONE; SPATHOLOBUS SUBERECTUS STEM; 3-HYDROXYTYROSOL 3-O-GLUCOSIDE

83781-011

Active Ingredient

Borneol 1.2%
Camphor 1.5%

Purpose

Topical Analgesic

Use

For sub healthy people with discomfort caused by neck, shoulder,waist and leg.

Warnings

For external use only.

When Using

use only as directed
do not bandage tighty or use with a heating pad
avoid contact with eves and mucous membranes
do not apply to wounds or damaged, broken or imitated skin
do not use at the same time as other topical analgesics

Keep Out Of Reach Of Children

Directions

adults and children over 12 years: After cleaning and drying the skin, peel off the protective liner of the patch and apply one patch to each knee once daily.
children 12 years or younger: ask a doctor

Other information

store at room temperature, not to exceed 86°F (30°C)

Inactive ingredients

Mugwort oil, sweet-scented osmanthus oil, eucalyptus oil, cinnamon, dried ginger, suberect, spatholobus stem, magnetic powder, kusnezoff monkshood root, herba speranskiae tuberculatae

Questions

Questions or comments?

Email: mqupin86@gmail.com